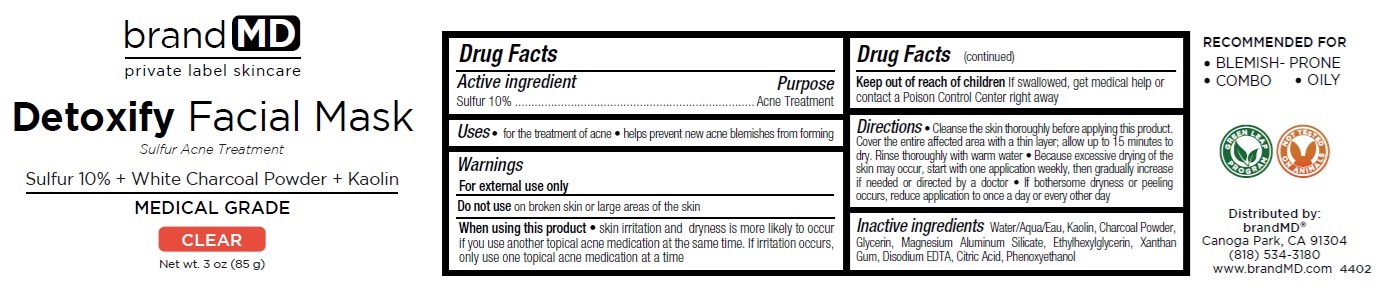 DRUG LABEL: Detoxify Facial Mask
NDC: 72957-007 | Form: GEL
Manufacturer: Private Label Skin Care
Category: otc | Type: HUMAN OTC DRUG LABEL
Date: 20250227

ACTIVE INGREDIENTS: SULFUR 10 g/100 g
INACTIVE INGREDIENTS: WATER; KAOLIN; ACTIVATED CHARCOAL; GLYCERIN; MAGNESIUM ALUMINUM SILICATE; ETHYLHEXYLGLYCERIN; XANTHAN GUM; EDETATE DISODIUM; CITRIC ACID MONOHYDRATE; PHENOXYETHANOL

Detoxify Facial Mask

Active ingredient

Sulfur 10%

Purpose

Acne Treatment

Uses

• for the treatment of acne
• helps prevent new acne blemishes from forming

Warnings

For external use only

Do not use on broken skin or large areas of the skin

When using this product • skin irritation and dryness is more likely to occur if you use another topical acne medication at the same time. If irritation occurs, only use one topical acne medication at a time

Keep out of reach of children If swallowed, get medical help or contact a Poison Control Center right away

Directions

• Cleanse the skin thoroughly before applying this product. Cover the entire affected area with a thin layer; allow up to 15 minutes to dry. Rinse thoroughly with warm water • Because excessive drying of the skin may occur, start with one application weekly, then gradually increase if needed or directed by a doctor • If bothersome dryness or peeling occurs, reduce application to once a day or every other day

Inactive ingredients

Water/Aqua/Eau, Kaolin, Charcoal Powder, Glycerin, Magnesium Aluminum Silicate, Ethylhexylglycerin, Xanthan Gum, Disodium EDTA, Citric Acid, Phenoxyethanol

brand MD

Sulfur 10% + White Charcoal Powder + Kaolin

MEDICAL GRADE

CLEAR

RECOMMENDED FOR
• BLEMISH- PRONE
• COMBO • OILY

GREEN LEAF PROGRAM

NOT TESTED ON ANIMALS

Distributed by:
brandMD®
Canoga Park, CA 91304
(818) 534-3180
www.brandMD.com